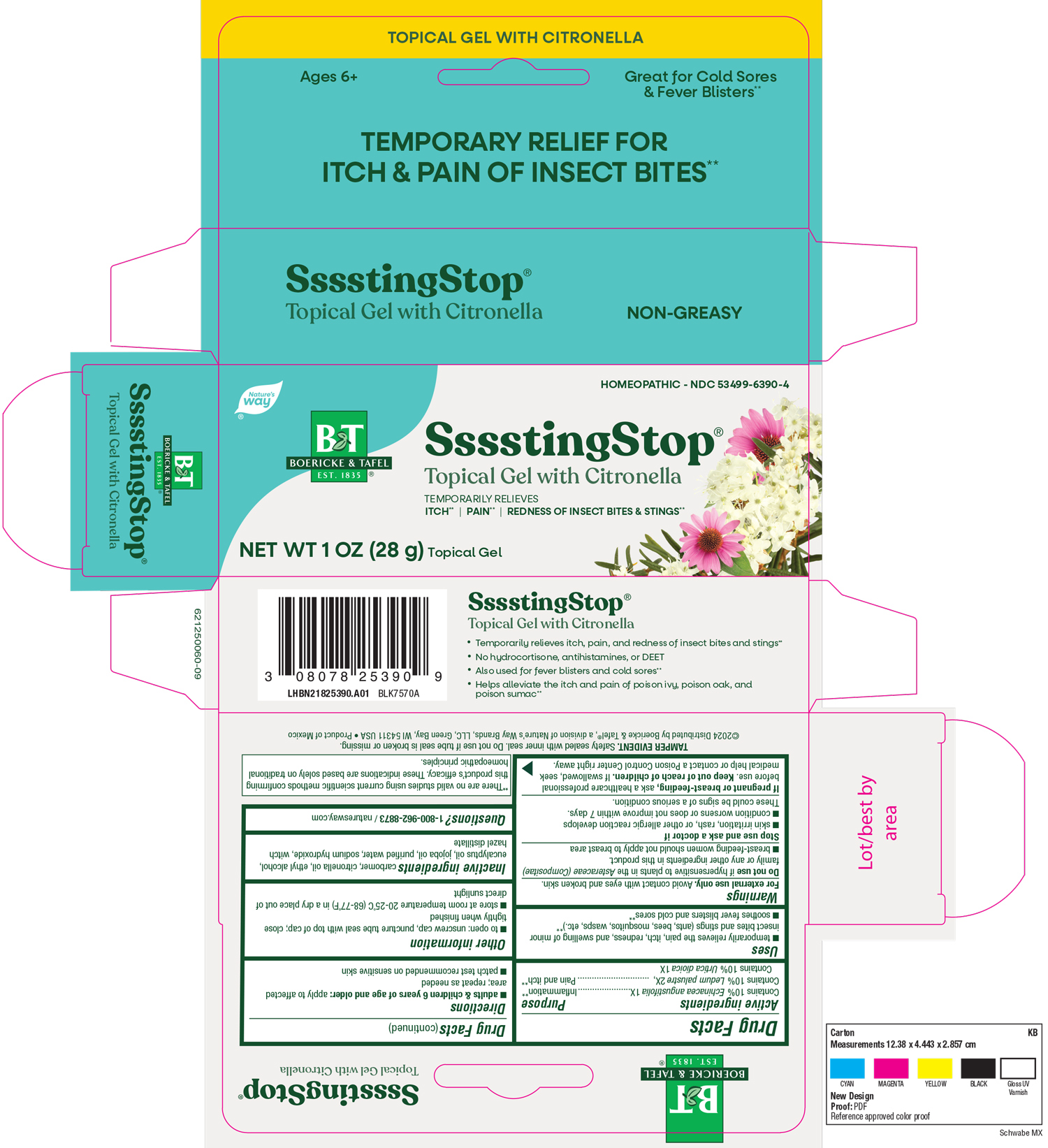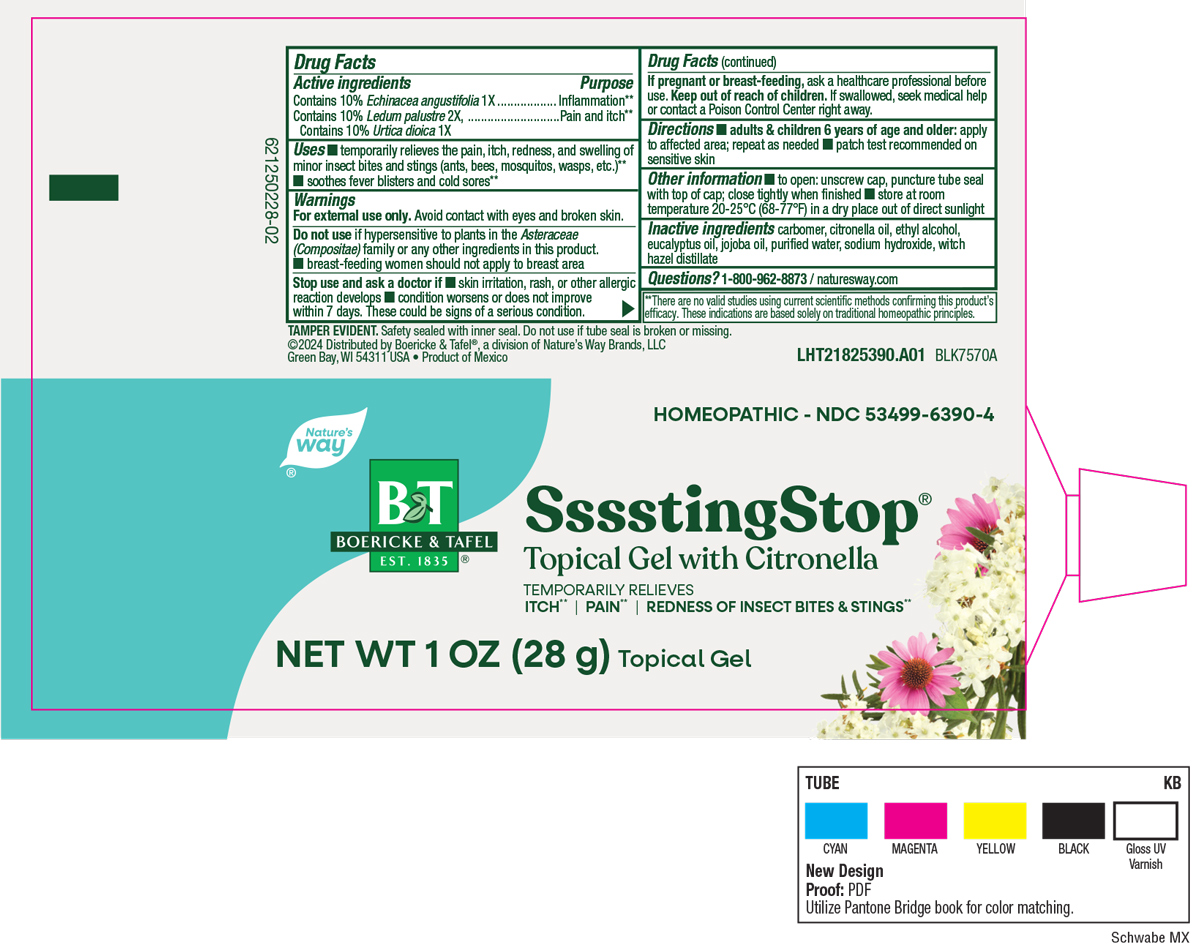 DRUG LABEL: Ssssting Stop
NDC: 53499-6390 | Form: GEL
Manufacturer: Schwabe North America, Inc.
Category: homeopathic | Type: HUMAN OTC DRUG LABEL
Date: 20251118

ACTIVE INGREDIENTS: Echinacea Angustifolia 1 [hp_X]/78 g; Ledum Palustre Twig 2 [hp_X]/78 g; Urtica Dioica 1 [hp_X]/78 g
INACTIVE INGREDIENTS: CITRONELLA OIL; ALCOHOL; EUCALYPTUS OIL; JOJOBA OIL; CARBOMER HOMOPOLYMER TYPE C; WATER; SODIUM HYDROXIDE; WITCH HAZEL

SSSSTING STOP

Active Ingredients

Echinacia angustifoloia 1X

Ledum palustre 2X

Urtica dioica 1X

Inactive Ingredient

Carbomer

Citronella Oil

Ethyl Alcohol

Eucalyptus Oil

Jojoba Oil

Purified Water

Sodium Hydroxide

Witch Hazel Distillate

Indications & Usage

Temporarily relieves the pain, itch, redness, and swelling of minor insect bites and stings (ants, bees, mosquitos, wasps, etc).

Soothes fever blisters and cold sores.

Purpose

Temporarily relieves the pain, itch, redness, and swelling of minor insect bites and stings (ants, bees, mosquitos, wasps, etc).

Soothes fever blisters and cold sores.

Dosage & Administration

Directions:

Adults & children 6 years of age and older: Apply to affected area; repeat as needed.

Patch test recommended on sensitive skin.

Warnings

For external use only. Avoid contact with eyes and broken skin.

Do not use if hypersensitive to plants in the Asteraceae (Compositae) family or any other ingredients in this product.

Breast-feeding women should not apply to breast area.

Stop Use

Stop use and ask a doctor if skin irritation, rash, or other allergic reaction develops, condition worsens or does not improve within 7 days.

These could be signs of a serious condition.

Pregnancy or breast feeding

If pregnant or breast-feeding, ask a healthcare professional before use.

Keep out of reach of children

Overdosage

If swallowed, seek medical help or contact a Poison Control Center right away.